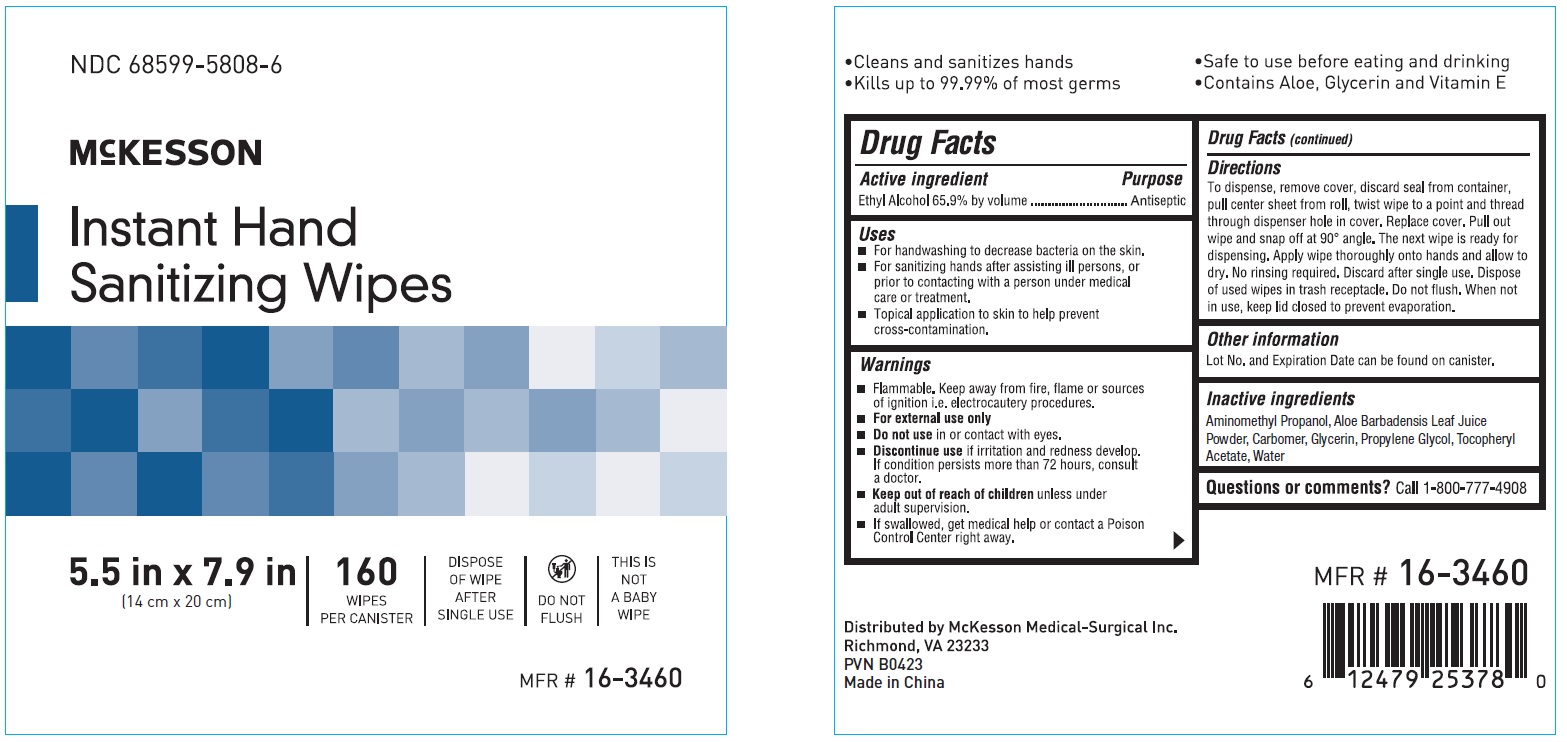 DRUG LABEL: Instant Hand Sanitizing Wipe
NDC: 68599-5808 | Form: SWAB
Manufacturer: McKesson
Category: otc | Type: HUMAN OTC DRUG LABEL
Date: 20241014

ACTIVE INGREDIENTS: ALCOHOL 65.9 mg/1 1
INACTIVE INGREDIENTS: AMINOMETHYLPROPANOL; ALOE; GLYCERIN; .ALPHA.-TOCOPHEROL ACETATE; CARBOMER HOMOPOLYMER, UNSPECIFIED TYPE; PROPYLENE GLYCOL; WATER

Instant Hand Sanitizing Wipe

Drug Facts

Active ingredient
Ethyl Alcohol 65.9% by volume

Purpose
Antiseptic

Uses

- For handwashing to decrease bacteria on the skin.
- For sanitizing hands after assisting ill persons, or Prior to contacting with a person under medical care or treatment
- Topical Application to skin to help prevent cross-contamination.

Warnings
Flammable. Keep away from fire, flame or source of ignition i.e. electrocautery procedures.
For external use only.

Do not use in or contact with eyes.
Discontinue use if irritation and redness develop. If condition persists more than 72 hours, consult a doctor.

KEEP OUT OF REACH OF CHILDREN

Keep out of reach of childrenunless under adult supervision.
if swallowed, get medical help or contact a Poison Control Center right away.

Directions
To dispense, remove cover, discard seal from container, pull center sheet from roll, twist wipe to a point and thread through dispenser hole in cover.
Replace cover. Pull out wipe and snap off at 90 degree angle. The next wipe is ready for dispensing. Apply wipe thoroughly onto hands and allow to dry.
No rinsing required. Discard after single use. Dispose of used wipes in trash receptacle. Do not flush. When not in use, keep lid closed to prevent evaporation.

Other information
Lot No. and Expiration Date can be found on canister.
Store at 53.6 - 93.2*F (12-34*C)

Inactive ingredients
Aminomethyl Propanol, Aloe, Barbadensis Leaft Powder, Carbomer, Glycerin, Propylene Glycol, Tocopheryl Acetate, Water

Questions?Call 1-800-777-4908

PACKAGE LABEL

McKesson

68599-5808-6
16-3460
Instant Hand Sanitizing Wipe
5.5 in x 7.9 in
(14 cm x 20 cm)

160 wipes per canister